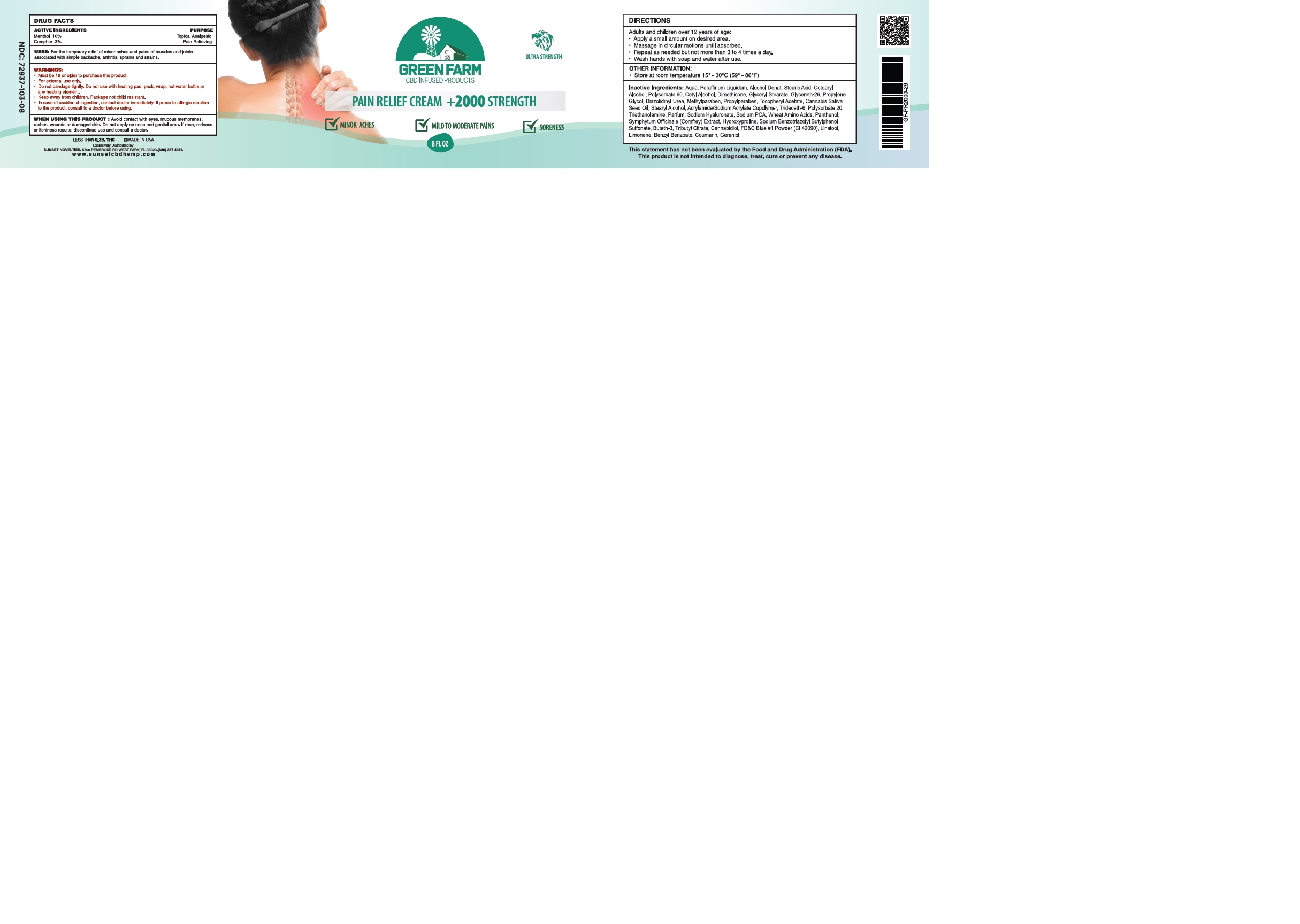 DRUG LABEL: MENTHOL, CAMPHOR
NDC: 72937-103 | Form: CREAM
Manufacturer: SUNSET NOVELTIES, INC
Category: otc | Type: HUMAN OTC DRUG LABEL
Date: 20251121

ACTIVE INGREDIENTS: MENTHOL 10 g/100 g; CAMPHOR (NATURAL) 3 g/100 g
INACTIVE INGREDIENTS: TRIBUTYL CITRATE; PANTHENOL; HYDROXYPROLINE; PROPYLPARABEN; STEARYL ALCOHOL; ACRYLIC ACID/SODIUM ACRYLATE COPOLYMER (1:1; 600 MPA.S AT 0.2%); GLYCERETH-26; DIAZOLIDINYL UREA; BUTETH-3; BASIC BLUE 1; WATER; STEARIC ACID; GLYCERYL STEARATE SE; METHYLPARABEN; CANNABIS SATIVA SEED OIL; TRIDECETH-6; POLYSORBATE 20; SODIUM BENZOTRIAZOLYL BUTYLPHENOL SULFONATE; POLYSORBATE 60; CETYL ALCOHOL; DIMETHICONE 1000

72937-103-08

ACTIVE INGREDIENT

Menthol 10%

Camphor 3%

PURPOSE

External Analgesic

Pain Relieving

USES:

For the temporary relief of minor aches and pains of muscles and joints associated with simple backache, arthritis, sprains and strains.

WARNINGS

For external use only.
Do not bandage tightly. Do not use with heating pad, pack, wrap, hot water bottle or any heating element.

In case of accidental ingestion, contact doctor immediately. If prone to allergic reaction to the product, consult to a doctor before using.

WHEN USING

Avoid contact with eyes, mucous membranes, rashes, wounds or damaged skin.
Do not apply on nose and genital area.

If rash, redness or itchiness results; discontinue use and consult a doctor.

DIRECTIONS:

Adults and children over 12 years of age; apply a thin layer to affected area and rub gently not more than 3 to 4 times a day.
Wash hands with soap and water after use.

Children under 12 years of age; do not use unless directed by doctor/physician

Keep away from children. Package not child resistant.

OTHER INFORMATION:

Store at room temperature 15° - 30°C (59° - 86°F)

INACTIVE INGREDIENT

Aqua, Paraffinum Liquidum, Alcohol Denat, Stearic Acid, Cetearyl Alcohol, Polysorbate 60, Cetyl Alcohol, Dimethicone, Glyceryl Stearate, Glycereth-26, Propylene Glycol, Diazolidinyl Urea, Methylparaben, Propylparaben, Tocopheryl Acetate, Cannabis Sativa Seed Oil, Stearyl Alcohol, Acrylamide/Sodium Acrylate Copolymer, Trideceth-6, Polysorbate 20, Triethanolamine, Parfum, Sodium Hyaluronate, Sodium PCA, Wheat Amino Acids, Panthenol, Symphytum Officinale (Comfrey) Extract, Hydroxyproline, Sodium Benzotriazolyl Butylphenol Sulfonate, Buteth-3, Tributyl Citrate, Cannabidiol, FD&C Blue #1 Powder (CI 42090), Linalool, Limonene, Benzyl Benzoate, Coumarin, Geraniol.